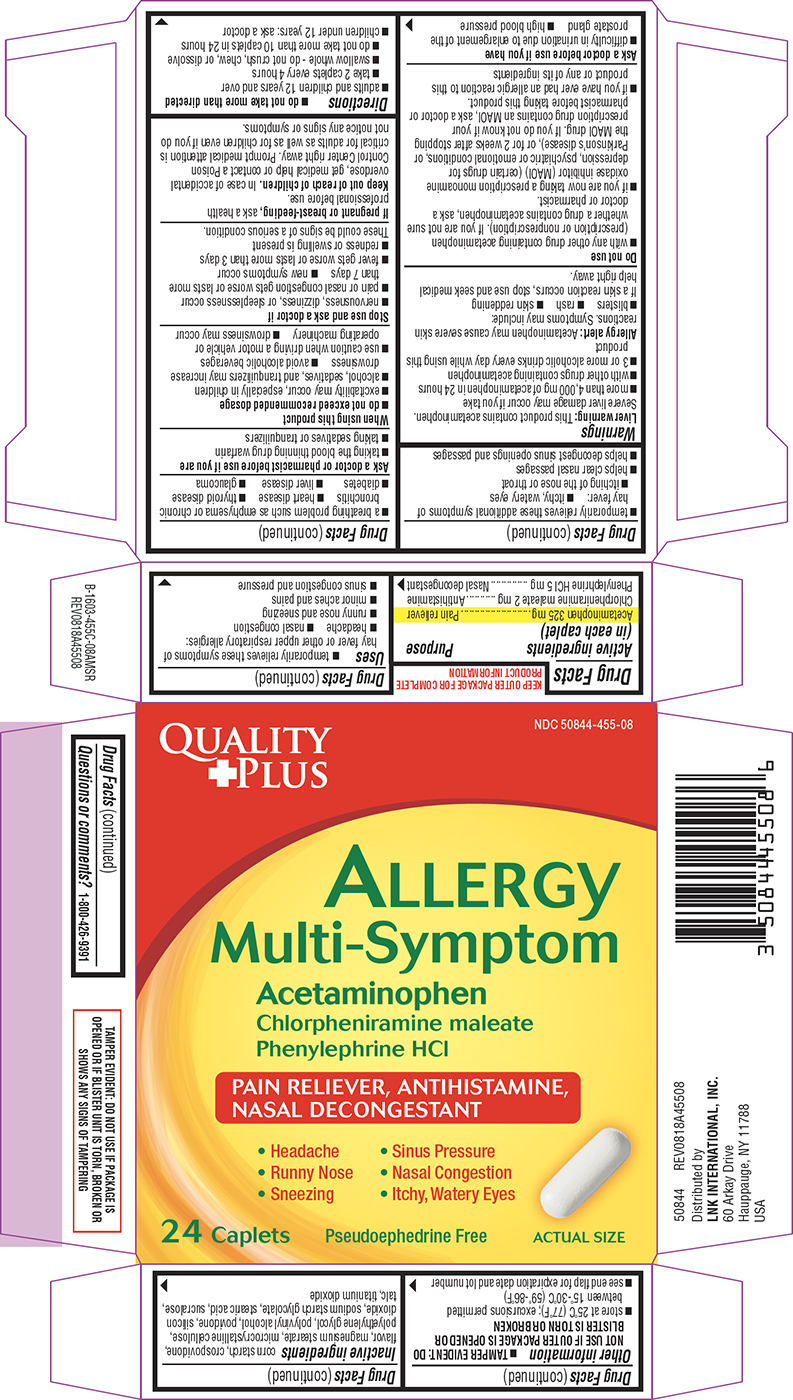 DRUG LABEL: Allergy
NDC: 50844-455 | Form: TABLET, FILM COATED
Manufacturer: L.N.K. International, Inc.
Category: otc | Type: HUMAN OTC DRUG LABEL
Date: 20260115

ACTIVE INGREDIENTS: ACETAMINOPHEN 325 mg/1 1; CHLORPHENIRAMINE MALEATE 2 mg/1 1; PHENYLEPHRINE HYDROCHLORIDE 5 mg/1 1
INACTIVE INGREDIENTS: STARCH, CORN; CROSPOVIDONE, UNSPECIFIED; MAGNESIUM STEARATE; MICROCRYSTALLINE CELLULOSE; POLYETHYLENE GLYCOL, UNSPECIFIED; POLYVINYL ALCOHOL, UNSPECIFIED; POVIDONE, UNSPECIFIED; SILICON DIOXIDE; SODIUM STARCH GLYCOLATE TYPE A POTATO; STEARIC ACID; SUCRALOSE; TALC; TITANIUM DIOXIDE

Quality Plus 44-455C-AMS

Active ingredients (in each caplet)

Acetaminophen 325 mg
Chlorpheniramine maleate 2 mg
Phenylephrine HCl 5 mg

Purpose

Pain reliever
Antihistamine
Nasal decongestant

Uses

- temporarily relieves these symptoms of hay fever or other upper respiratory allergies:
  - headache
  - nasal congestion
  - runny nose and sneezing
  - minor aches and pains
  - sinus congestion and pressure
- temporarily relieves these additional symptoms of hay fever:
  - itchy, watery eyes
  - itching of the nose or throat
- helps clear nasal passages
- helps decongest sinus openings and passages

Warnings

Liver warning: This product contains acetaminophen. Severe liver damage may occur if you take

- more than 4,000 mg of acetaminophen in 24 hours
- with other drugs containing acetaminophen
- 3 or more alcoholic drinks every day while using this product

Allergy alert: Acetaminophen may cause severe skin reactions. Symptoms may include:

- blisters
- rash
- skin reddening

If a skin reaction occurs, stop use and seek medical help right away.

Do not use

- with any other drug containing acetaminophen (prescription or nonprescription). If you are not sure whether a drug contains acetaminophen, ask a doctor or pharmacist.
- if you are now taking a prescription monoamine oxidase inhibitor (MAOI) (certain drugs for depression, psychiatric or emotional conditions, or Parkinson’s disease), or for 2 weeks after stopping the MAOI drug. If you do not know if your prescription drug contains an MAOI, ask a doctor or pharmacist before taking this product.
- if you have ever had an allergic reaction to this product or any of its ingredients

Ask a doctor before use if you have

- difficulty in urination due to enlargement of the prostate gland
- high blood pressure
- a breathing problem such as emphysema or chronic bronchitis
- heart disease
- thyroid disease
- diabetes
- liver disease
- glaucoma

Ask a doctor or pharmacist before use if you are

- taking the blood thinning drug warfarin
- taking sedatives or tranquilizers

When using this product

- do not exceed recommended dosage
- excitability may occur, especially in children
- alcohol, sedatives, and tranquilizers may increase drowsiness
- avoid alcoholic beverages
- use caution when driving a motor vehicle or operating machinery
- drowsiness may occur

Stop use and ask a doctor if

- nervousness, dizziness, or sleeplessness occur
- pain or nasal congestion gets worse or lasts more than 7 days
- new symptoms occur
- fever gets worse or lasts more than 3 days
- redness or swelling is present

These could be signs of a serious condition.

If pregnant or breast-feeding,

ask a health professional before use.

Keep out of reach of children.

In case of accidental overdose, get medical help or contact a Poison Control Center right away. Prompt medical attention is critical for adults as well as for children even if you do not notice any signs or symptoms.

Directions

- do not take more than directed
- adults and children 12 years and over
  - take 2 caplets every 4 hours
  - swallow whole - do not crush, chew, or dissolve
  - do not take more than 10 caplets in 24 hours
- children under 12 years: ask a doctor

Other information

- TAMPER EVIDENT: DO NOT USE IF OUTER PACKAGE IS OPENED OR BLISTER IS TORN OR BROKEN
- store at 25°C (77°F); excursions permitted between 15°-30°C (59°-86°F)
- see end flap for expiration date and lot number

Inactive ingredients

corn starch, crospovidone, flavor, magnesium stearate, microcrystalline cellulose, polyethylene glycol, polyvinyl alcohol, povidone, silicon dioxide, sodium starch glycolate, stearic acid, sucralose, talc, titanium dioxide

Questions or comments?

1-800-426-9391

Principal Display Panel

QUALITY
+ PLUS

NDC 50844-455-08

Allergy
Multi-Symptom

Acetaminophen
Chlorpheniramine maleate
Phenylephrine HCl

PAIN RELIEVER, ANTIHISTAMINE,
NASAL DECONGESTANT

• Headache • Sinus Pressure
• Runny Nose • Nasal Congestion
• Sneezing • Itchy, Watery Eyes

24 Caplets

Pseudoephedrine Free

ACTUAL SIZE

TAMPER EVIDENT: DO NOT USE IF PACKAGE IS
OPENED OR IF BLISTER UNIT IS TORN, BROKEN OR
SHOWS ANY SIGNS OF TAMPERING

50844 REV0818A45508

Distributed by
LNK INTERNATIONAL, INC.
60 Arkay Drive
Hauppauge, NY 11788
USA

Quality Plus 44-455C-AMS